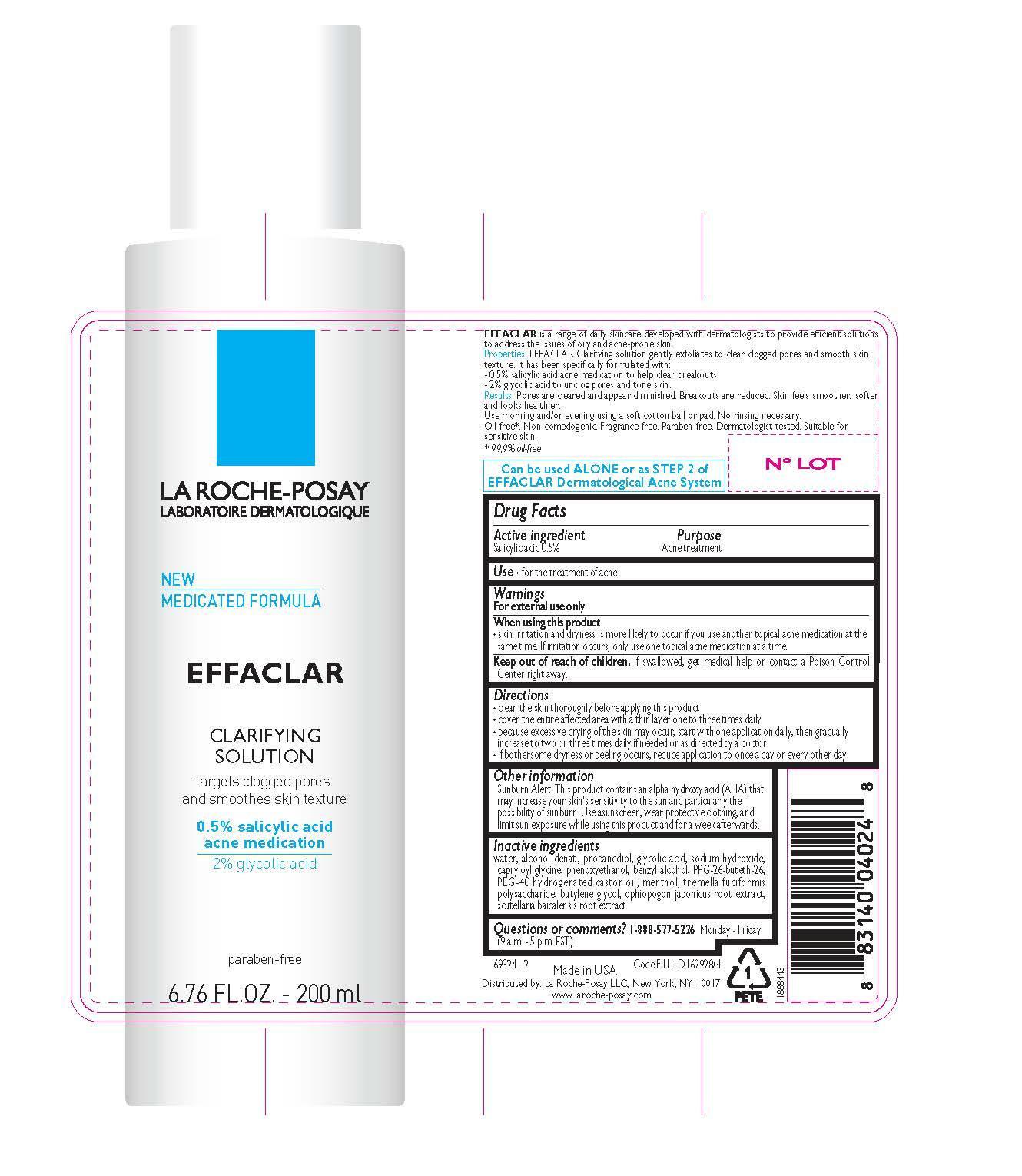 DRUG LABEL: La Roche Posay Laboratoire Dermatologique Effaclar Clarifying
NDC: 49967-024 | Form: SOLUTION
Manufacturer: L'Oreal USA Products Inc
Category: otc | Type: HUMAN OTC DRUG LABEL
Date: 20240101

ACTIVE INGREDIENTS: SALICYLIC ACID 5 mg/1 mL
INACTIVE INGREDIENTS: water; ALCOHOL; PROPANEDIOL; GLYCOLIC ACID; SODIUM HYDROXIDE; CAPRYLOYL GLYCINE; PHENOXYETHANOL; BENZYL ALCOHOL; PPG-26-BUTETH-26; MENTHOL; BUTYLENE GLYCOL

Drug Facts

Active ingredient

Salicylic acid 0.5%

Purpose

Acne treatment

Use

for the treatment of acne

Warnings

For external use only

When using this product

skin irritation and dryness is more likely to occur if you use another topical acne medication at the same time. If irritation occurs, only use one topical acne medication at a time.

Keep out of reach of children.

If swallowed, get medical help or contact a Poison Control Center right away.

Directions

- clean the skin thoroughly before applying this product
- cover the entire affected area with a thin layer one to three times daily
- because excessive drying of the skin may occur, start with one application daily, then gradually increase to two or three times daily if needed or as directed by a doctor
- if bothersome dryness or peeling occurs, reduce application to once a day or every other day

Other information

Sunburn Alert: This product contains an alpha hydroxy acid (AHA) that may increase your skin's sensitivity to the sun and particularly the possibility of sunburn. Use a sunscreen, wear protective clothing, and limit sun exposure while using this product and for a week afterwards.

Inactive ingredients

water, alcohol denat., propanediol, glycolic acid, sodium hydroxide, capryloyl glycine, phenoxyethanol, benzyl alcohol, PPG-26-buteth-26, PEG-40 hydrogenated castor oil, menthol, tremella fuciformis polysaccharide, butylene glycol, ophiopogon japonicus root extract, scutellaria baicalensis root extract

Questions or comments?

1-888-577-5226 Monday - Friday (9 a.m. - 5 p.m. EST)